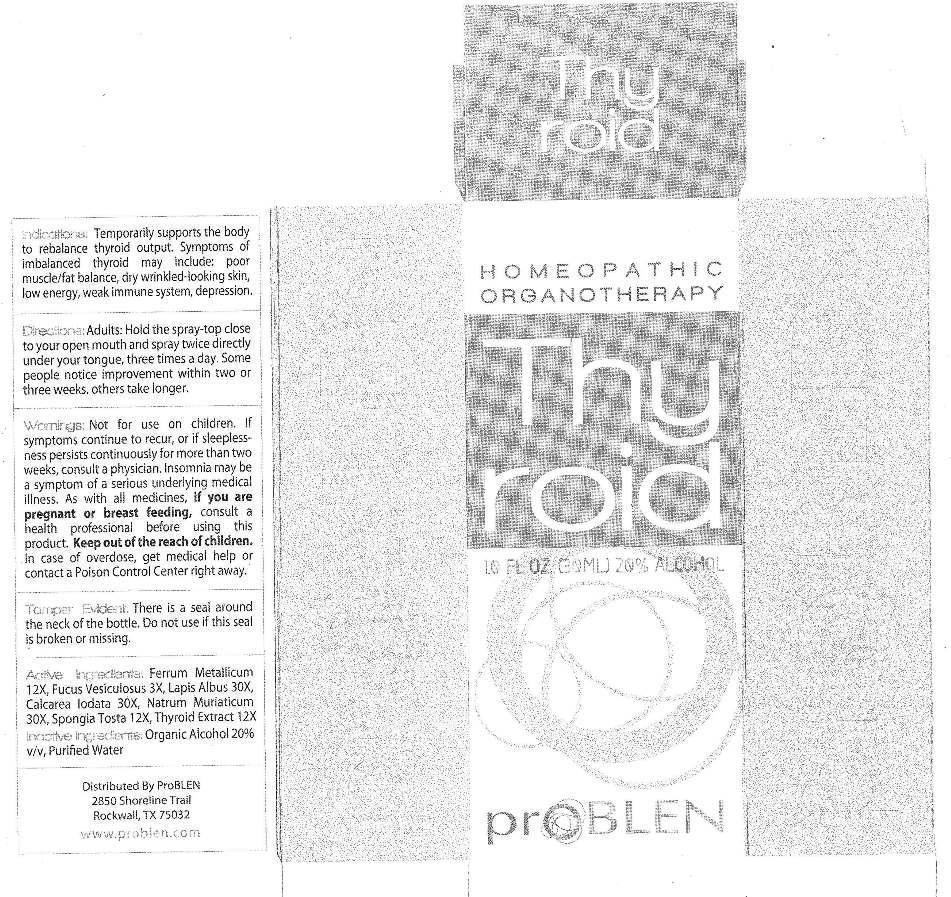 DRUG LABEL: Thyroid
NDC: 43853-0006 | Form: LIQUID
Manufacturer: ProBLEN
Category: homeopathic | Type: HUMAN OTC DRUG LABEL
Date: 20130307

ACTIVE INGREDIENTS: CALCIUM IODIDE 30 [hp_X]/1 mL; IRON 12 [hp_X]/1 mL; FUCUS VESICULOSUS 3 [hp_X]/1 mL; CALCIUM HEXAFLUOROSILICATE 30 [hp_X]/1 mL; SODIUM CHLORIDE 30 [hp_X]/1 mL; SPONGIA OFFICINALIS SKELETON, ROASTED 12 [hp_X]/1 mL; SUS SCROFA THYROID 12 [hp_X]/1 mL
INACTIVE INGREDIENTS: WATER; ALCOHOL

Drug Facts

ACTIVE INGREDIENTS

Calcarea Iodata 30X, Ferrum Metallicum 12X, Fucus Vesiculosus 3X, Lapis Albus 30X, Natrum Muriaticum 30X, Spongia Tosta 12X, Thyroidinum (Suis) 12X

INDICATIONS

Temporarily supports the body to rebalance thyroid output. Symptoms of imbalanced thyroid may include: poor muscle/fat balance, dry wrinkled-looking skin, low energy, weak immune system, depression.

WARNINGS

Not for use on children. If symptoms continue to recur, or if sleeplessness persists continuously for more than two weeks, consult a physician. Insomnia may be a symptom of a serious underlying medical illness. As with all medicines, if you are pregnant or breast feeding, consult a health professional before using this product. Keep out of reach of children. In case of overdose, get medical help or contact a Poison Control Center right away.

Tamper Evident: There is a seal around the neck of the bottle. Do not use if seal is broken or missing.

DIRECTIONS

Adults: Hold the sprag-top close to your open mouth and spray twice directly under your tongue, three times a day. Some people notice improvement within two or three weeks, others take longer.

INACTIVE INGREDIENTS

Purified Water, Organic Ethanol 20%

KEEP OUT OF REACH OF CHILDREN

In case of overdose, get medical help or contact a Poison Control Center right away.

INDICATIONS AND USAGE

Temporarily supports the body to rebalance thyroid output. Symptoms of imbalanced thyroid may include: poor muscle/fat balance, dry wrinkled-looking skin, low energy, weak immune system, depression.

QUESTIONS

Distributed by

ProBLEN (888) 326-2121 www.problen.com

2850 Shoreline Trail

Rockwall, TX 75032

PACKAGE LABEL

HOMEOPATHIC

ORGANOTHERAPY

10 FL OZ. (30ML)